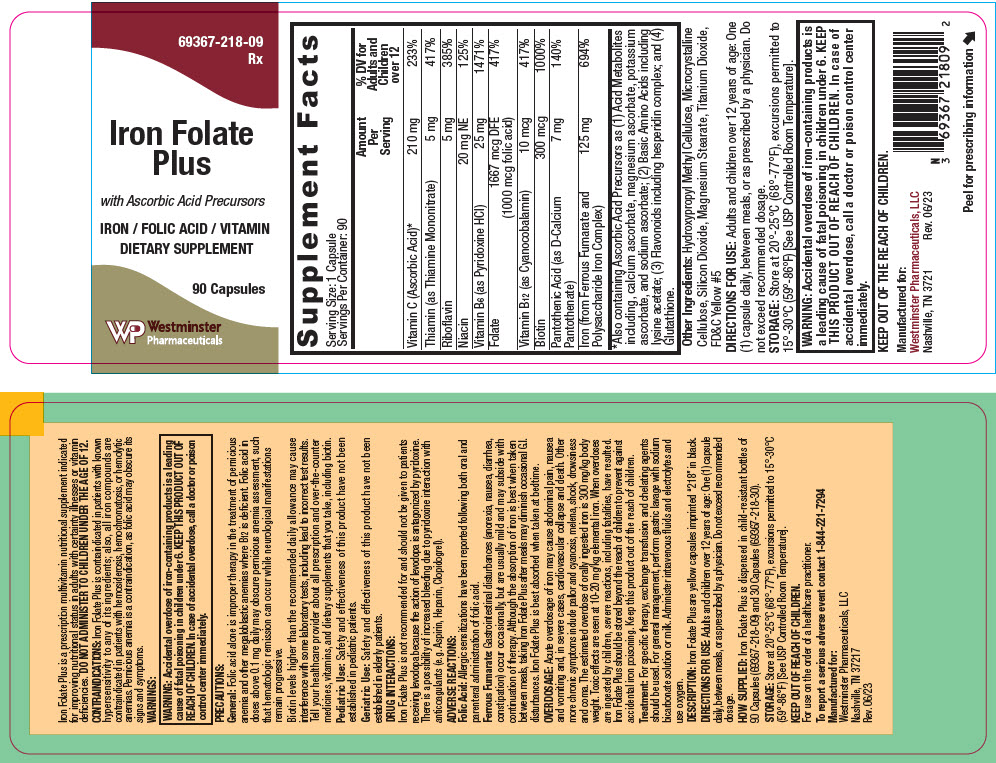 DRUG LABEL: Iron Folate Plus
NDC: 69367-218 | Form: CAPSULE
Manufacturer: Westminster Pharmaceuticals, LLC
Category: other | Type: DIETARY SUPPLEMENT
Date: 20230719

ACTIVE INGREDIENTS: FERROUS FUMARATE 62.5 mg/1 1; IRON 62.5 mg/1 1; ASCORBIC ACID 210 mg/1 1; THIAMINE MONONITRATE 5 mg/1 1; RIBOFLAVIN 5 mg/1 1; NIACIN 20 mg/1 1; PYRIDOXINE HYDROCHLORIDE 25 mg/1 1; FOLIC ACID 1 mg/1 1; CYANOCOBALAMIN 10 ug/1 1; BIOTIN 300 ug/1 1; CALCIUM PANTOTHENATE 7 mg/1 1
INACTIVE INGREDIENTS: HYPROMELLOSE, UNSPECIFIED; MICROCRYSTALLINE CELLULOSE; SILICON DIOXIDE; MAGNESIUM STEARATE; TITANIUM DIOXIDE; FD&C YELLOW NO. 5

Iron Folate Plus

STATEMENT OF IDENTITY

Supplement Facts
Serving Size: 1 Capsule
Servings Per Container: 90
 | Amount Per Serving | % DV for Adults and Children over 12
Vitamin C (Ascorbic Acid) [Also containing Ascorbic Acid Precursors as (1) Acid Metabolites including, calcium ascorbate, magnesium ascorbate, potassium ascorbate, and sodium ascorbate; (2) Basic Amino Acids including lysine acetate; (3) Flavonoids including hesperidin complex; and (4) Glutathione.] | 210 mg | 233%
Thiamin (as Thiamine Mononitrate) | 5 mg | 417%
Riboflavin | 5 mg | 385%
Niacin | 20 mg | NE 125%
Vitamin B6 (as Pyridoxine HCI) | 25 mg | 1471%
Folate | 1667 mcg DFE (1000 mcg folic acid) | 417%
Vitamin B12 (as Cyanocobalamin) | 10 mcg | 417%
Biotin | 300 mcg | 1000%
Pantothenic Acid (as D-Calcium Pantothenate) | 7 mg | 140%
Iron (from Ferrous Fumarate and Polysaccharide Iron Complex) | 125 mg | 694%

Other Ingredients: Hydroxypropyl Methyl Cellulose, Microcrystalline Cellulose, Silicon Dioxide, Magnesium Stearate, Titanium Dioxide, FD&C Yellow #5

HEALTH CLAIM

Iron Folate Plus is a prescription multivitamin nutritional supplement indicated for improving nutritional status in adults with certainty illnesses or vitamin deficiencies. DO NOT ADMINISTER TO CHILDREN UNDER THE AGE OF 12.

CONTRAINDICATIONS

Iron Folate Plus is contraindicated in patients with known hypersensitivity to any of its ingredients; also, all iron compounds are contraindicated in patients with hemosiderosis, hemochromatosis, or hemolytic anemias. Pernicious anemia is a contraindication, as folic acid may obscure its signs and symptoms.

WARNINGS

WARNING: Accidental overdose of iron-containing products is a leading cause of fatal poisoning in children under 6. KEEP THIS PRODUCT OUT OF REACH OF CHILDREN. In case of accidental overdose, call a doctor or poison control center immediately.

PRECAUTIONS

General

Folic acid alone is improper therapy in the treatment of pernicious anemia and other megaloblastic anemias where B12 is deficient. Folic acid in doses above 0.1 mg daily may obscure pernicious anemia assessment, such that hematologic remission can occur while neurological manifestations remain progressive.

Biotin levels higher than the recommended daily allowance may cause interference with some laboratory tests, including lead to incorrect test results. Tell your healthcare provider about all prescription and over-the-counter medicines, vitamins, and dietary supplements that you take, including biotin.

Pediatric Use

Safety and effectiveness of this product have not been established in pediatric patients.

Geriatric Use

Safety and effectiveness of this product have not been established in elderly patients.

DRUG INTERACTIONS

Iron Folate Plus is not recommended for and should not be given to patients receiving levodopa because the action of levodopa is antagonized by pyridoxine. There is a possibility of increased bleeding due to pyridoxine interaction with anticoagulants (e.g. Aspirin, Heparin, Clopidogrel).

ADVERSE REACTIONS

Folic Acid

Allergic sensitizations have been reported following both oral and parenteral administration of folic acid.

Ferrous Fumarate

Gastrointestinal disturbances (anorexia, nausea, diarrhea, constipation) occur occasionally, but are usually mild and may subside with continuation of therapy. Although the absorption of iron is best when taken between meals, taking Iron Folate Plus after meals may diminish occasional G.I. disturbances. Iron Folate Plus is best absorbed when taken at bedtime.

OVERDOSAGE

Acute overdosage of iron may cause abdominal pain, nausea and vomiting and, in severe cases, cardiovascular collapse and death. Other more chronic symptoms include pallor and cyanosis, melena, shock, drowsiness and coma. The estimated overdose of orally ingested iron is 300 mg/kg body weight. Toxic effects are seen at 10-20 mg/kg elemental iron. When overdoses are ingested by children, severe reactions, including fatalities, have resulted. Iron Folate Plus should be stored beyond the reach of children to prevent against accidental iron poisoning. Keep this product out of the reach of children.

Treatment

For specific therapy, exchange transfusion and chelating agents should be used. For general management, perform gastric lavage with sodium bicarbonate solution or milk. Administer intravenous fluids and electrolytes and use oxygen.

DESCRIPTION

Iron Folate Plus are yellow capsules imprinted "218" in black.

DIRECTIONS FOR USE

Adults and children over 12 years of age: One (1) capsule daily, between meals, or as prescribed by a physician. Do not exceed recommended dosage.

HOW SUPPLIED

Iron Folate Plus is dispensed in child-resistant bottles of 90 Capsules (69367-218-09) and 30 Capsules (69367-218-30).

STORAGE

Store at 20°-25°C (68°-77°F), excursions permitted to 15°-30°C (59°-86°F) [See USP Controlled Room Temperature].

KEEP OUT OF REACH OF CHILDREN.

For use on the order of a healthcare practitioner.

HEALTH CLAIM

To report a serious adverse event contact 1-844-221-7294

Manufactured for:
Westminster Pharmaceuticals, LLC
Nashville, TN 37217
Rev. 06/23

PRINCIPAL DISPLAY PANEL - 90 Capsule Bottle Label

69367-218-09
Rx

Iron Folate
Plus

with Ascorbic Acid Precursors

IRON / FOLIC ACID / VITAMIN
DIETARY SUPPLEMENT

90 Capsules

Westminster
Pharmaceuticals